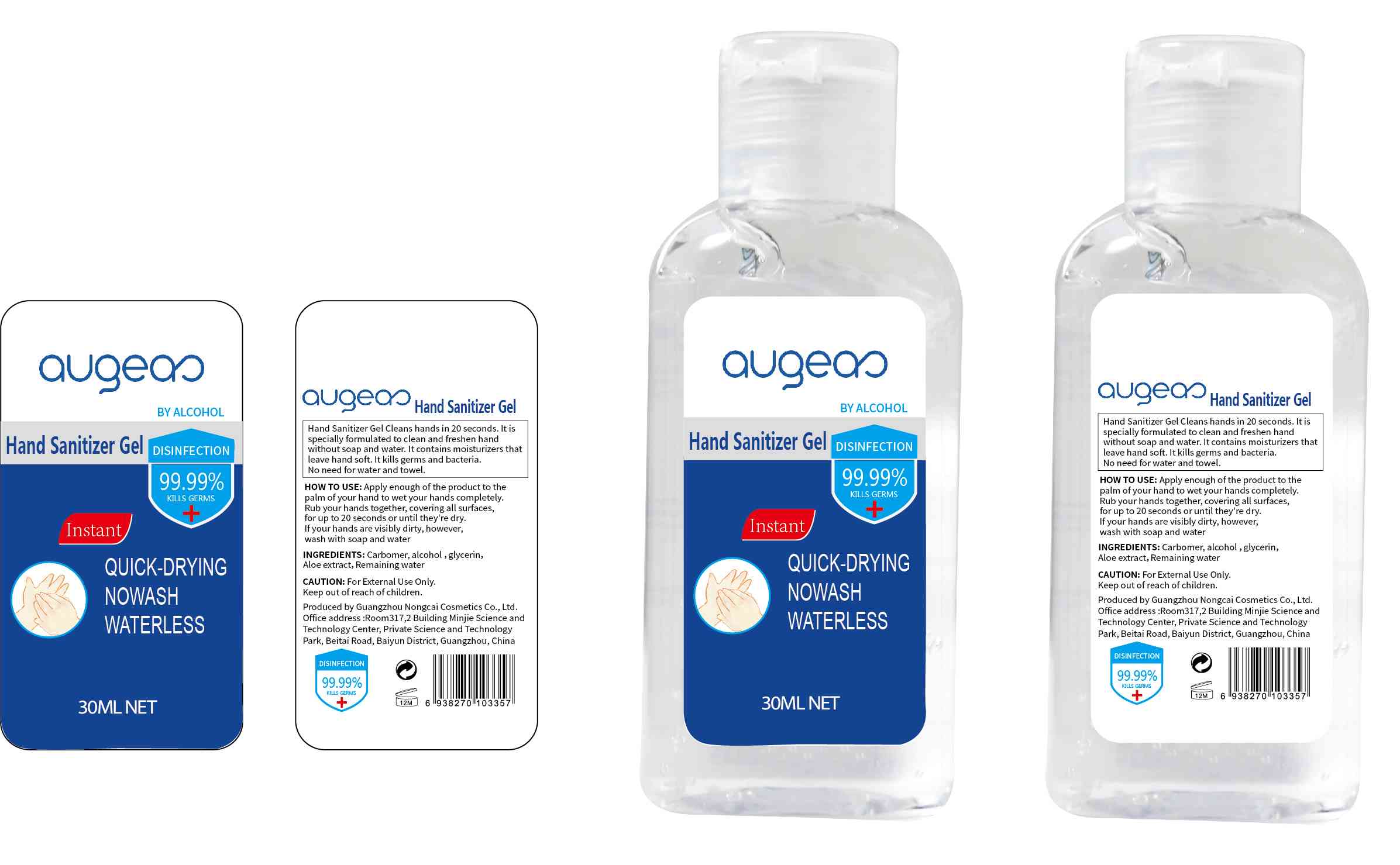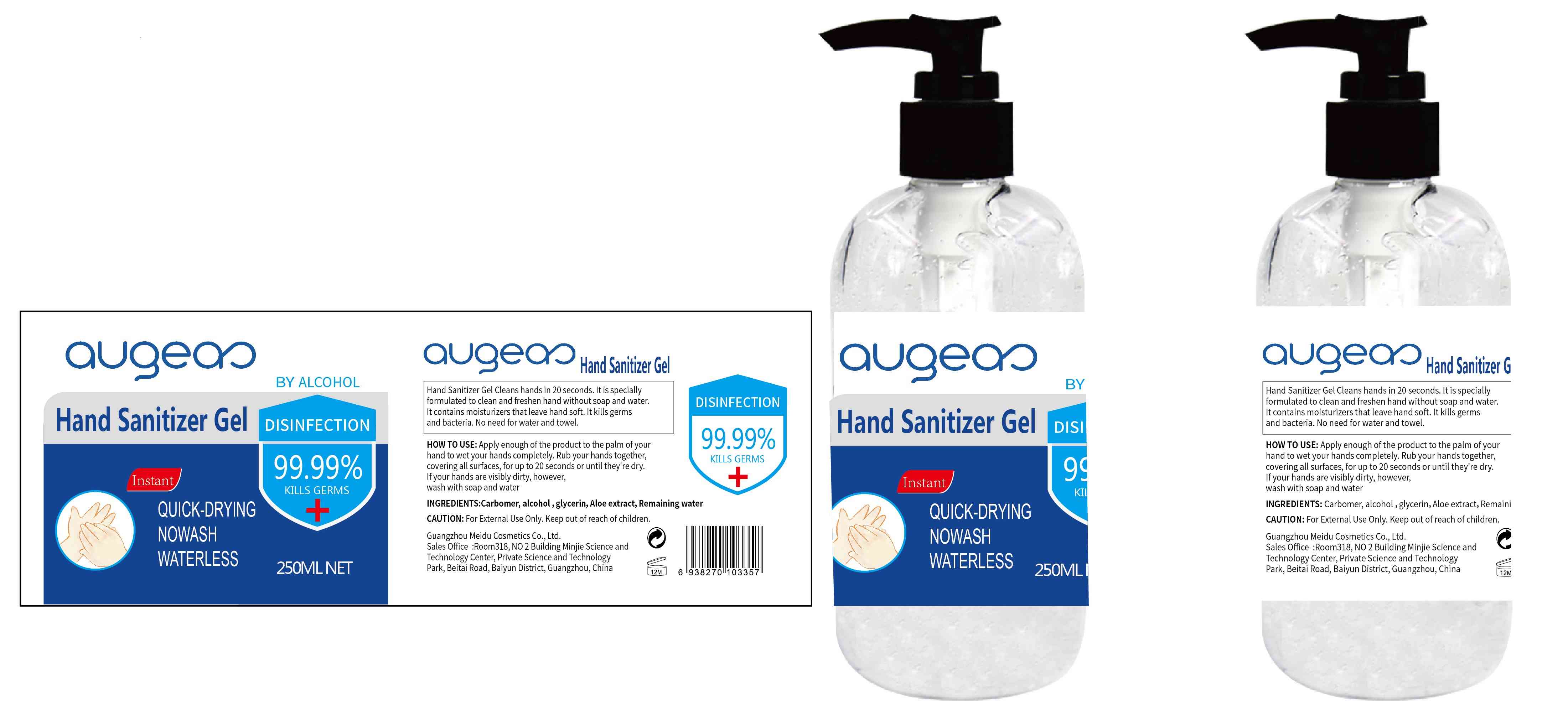 DRUG LABEL: Hand Sanitizer
NDC: 76599-011 | Form: GEL
Manufacturer: Guangzhou Meidu Cosmetics Co.,Ltd.
Category: otc | Type: HUMAN OTC DRUG LABEL
Date: 20201124

ACTIVE INGREDIENTS: ALCOHOL 60 mL/100 mL
INACTIVE INGREDIENTS: ALOE; GLYCERIN; CARBOMER HOMOPOLYMER, UNSPECIFIED TYPE; WATER

76599-011
Hand Sanitizer Gel

Active Ingredient(s)

Alcohol 60% V/V

Purpose

/

Use

Hand Sanitizer Gel Cleans hands in 20 seconds. It is specially formulated to clean and freshen hand without soap and water.

It contains moisturizers that leave hand soft. It kills germs and bacteria. No need for water and towel.

Warnings

For External Use Only. Keep out of reach of children.

Do not use

/

WHEN USING

/

STOP USE

/

Keep out of reach of children.

Directions

Apply enough of the product to the palm of your hand to wet your hands completely. Rub your hands together, covering all surfaces, for up to 20 seconds or until they're dry.

If your hands are visibly dirty, however, wash with soap and water

Other information

/

Inactive ingredients

Carbomer, glycerinl, Aloe extract, Remaining water